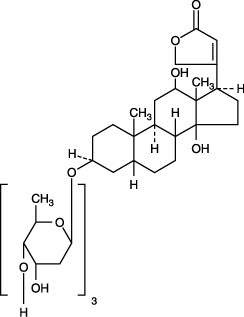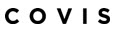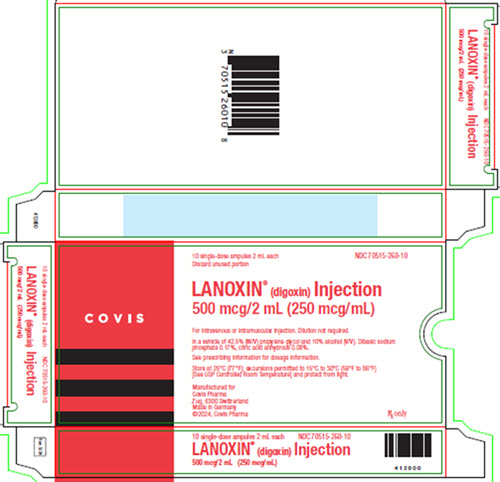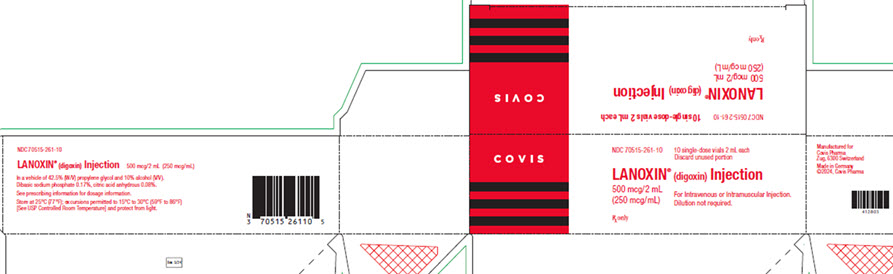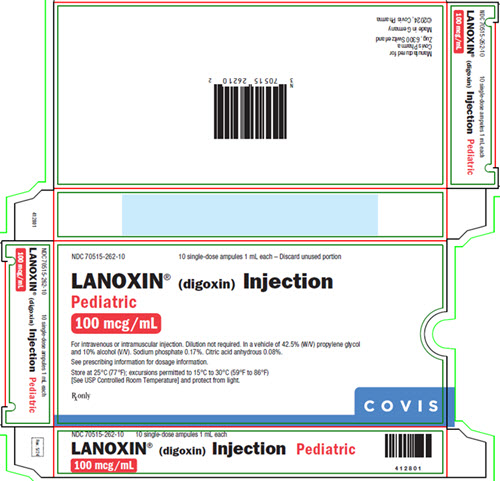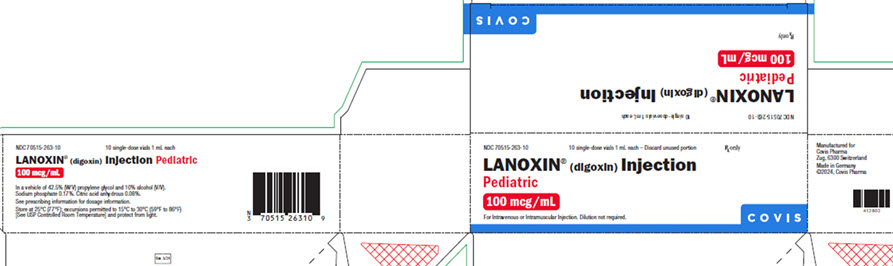 DRUG LABEL: LANOXIN
NDC: 70515-260 | Form: INJECTION, SOLUTION
Manufacturer: Covis Pharma US, Inc
Category: prescription | Type: HUMAN PRESCRIPTION DRUG LABEL
Date: 20251017

ACTIVE INGREDIENTS: DIGOXIN 250 ug/1 mL
INACTIVE INGREDIENTS: PROPYLENE GLYCOL; ALCOHOL; SODIUM PHOSPHATE, DIBASIC, UNSPECIFIED FORM; ANHYDROUS CITRIC ACID

HIGHLIGHTS OF PRESCRIBING INFORMATION

These highlights do not include all the information needed to use LANOXIN safely and effectively. See full prescribing information for LANOXIN.
LANOXIN®(digoxin) injection, for intravenous or intramuscular use
Initial U.S. Approval: 1954

1 INDICATIONS AND USAGE

LANOXIN is a cardiac glycoside indicated for:

- Treatment of mild to moderate heart failure in adults. (1.1)
- Increasing myocardial contractility in pediatric patients with heart failure. (1.2)
- Control of resting ventricular rate in adults with chronic atrial fibrillation. (1.3)

2 DOSAGE AND ADMINISTRATION

LANOXIN dose is based on patient-specific factors (age, lean body weight, renal function, etc.). See full prescribing information. Monitor for toxicity and therapeutic effect. (2)

Intravenous administration is preferable to intramuscular. Avoid bolus administration. (2)

3 DOSAGE FORMS AND STRENGTHS

LANOXIN®Injection: 500 mcg/2 mL (250 mcg/mL) single-dose ampule (3)
LANOXIN®Injection:500 mcg/2 mL (250 mcg/mL) single-dose vial (3)

LANOXIN®Injection Pediatric: 100 mcg/mL single-dose ampule (3)
LANOXIN®Injection Pediatric: 100 mcg/mL single-dose vial (3)

4 CONTRAINDICATIONS

- Ventricular fibrillation. (4)
- Known hypersensitivity to digoxin or other forms of digitalis. (4)

5 WARNINGS AND PRECAUTIONS

- Risk of rapid ventricular response leading to ventricular fibrillation in patients with AV accessory pathway. (5.1)
- Risk of advanced or complete heart block in patients with sinus node disease and AV block. (5.2)
- Digoxin toxicity: Indicated by nausea, vomiting, visual disturbances, and cardiac arrhythmias. Advanced age, low body weight, impaired renal function and electrolyte abnormalities predispose to toxicity. (5.3)
- Risk of ventricular arrhythmias during electrical cardioversion. (5.4)
- Not recommended in patients with acute myocardial infarction (5.5)
- Avoid LANOXIN in patients with myocarditis. (5.6)

6 ADVERSE REACTIONS

The overall incidence of adverse reactions with digoxin has been reported as 5-20%, with 15-20% of adverse events considered serious. Cardiac toxicity accounts for about one-half, gastrointestinal disturbances for about one-fourth, and CNS and other toxicity for about one-fourth of these adverse events. (6.1)

To report SUSPECTED ADVERSE REACTIONS, contact Covis Pharma at 1-877-411-2510 or FDA at 1-800-FDA-1088 or www.fda.gov/medwatch

7 DRUG INTERACTIONS

- PGP Inducers/Inhibitors: Drugs that induce or inhibit PGP have the potential to alter digoxin pharmacokinetics. (7.1)
- The potential for drug-drug interactions must be considered prior to and during drug therapy. See full prescribing information. (7.2, 7.3, 12.3)

8 USE IN SPECIFIC POPULATIONS

- Pediatric patients: Newborn infants display variability in tolerance to LANOXIN. (8.4)
- Geriatric patients: Consider renal function in dosage selection, and carefully monitor for side effects. (8.5)
- Renal impairment: LANOXIN is excreted by the kidneys. Consider renal function during dosage selection. (8.6)

FULL PRESCRIBING INFORMATION

1 INDICATIONS AND USAGE

1.1 Heart Failure in Adults

LANOXIN is indicated for the treatment of mild to moderate heart failure in adults. LANOXIN increases left ventricular ejection fraction and improves heart failure symptoms, as evidenced by improved exercise capacity and decreased heart failure-related hospitalizations and emergency care, while having no effect on mortality. Where possible, LANOXIN should be used in combination with a diuretic and an angiotensin-converting enzyme (ACE) inhibitor.

1.2 Heart Failure in Pediatric Patients

LANOXIN increases myocardial contractility in pediatric patients with heart failure.

1.3 Atrial Fibrillation in Adults

LANOXIN is indicated for the control of ventricular response rate in adult patients with chronic atrial fibrillation.

2 DOSAGE AND ADMINISTRATION

2.1 Important Dosing and Administration Information

In selecting a LANOXIN dosing regimen, it is important to consider factors that affect digoxin blood levels (e.g., body weight, age, renal function, concomitant drugs) since toxic levels of digoxin are only slightly higher than therapeutic levels. Dosing can be either initiated with a loading dose followed by maintenance dosing if rapid titration is desired orinitiated with maintenance dosing without a loading dose.

Parenteral administration of digoxin should be used only when the need for rapid digitalization is urgent or when the drug cannot be taken orally. Intramuscular injection can lead to severe pain at the injection site, thus intravenous administration is preferred. If the drug must be administered by the intramuscular route, it should be injected deep into the muscle followed by massage. For adults, no more than 500 mcg of LANOXIN Injection should be injected into a single site. For pediatric patients, no more than 200 mcg of LANOXIN Injection Pediatric should be injected into a single site.

Administer the dose over a period of 5 minutes or longer and avoid bolus administration to prevent systemic and coronary vasoconstriction. Mixing of LANOXIN Injection and Injection Pediatric with other drugs in the same container or simultaneous administration in the same intravenous line is not recommended.

LANOXIN Injection and Injection Pediatric can be administered undiluted or diluted with a 4-fold or greater volume of Sterile Water for Injection, 0.9% Sodium Chloride Injection, or 5% Dextrose Injection. The use of less than a 4-fold volume of diluent could lead to precipitation of the digoxin. Immediate use of the diluted product is recommended.

Consider interruption or reduction in LANOXIN dose prior to electrical cardioversion [see Warnings and Precautions (5.4)].

Discard unused portion of LANOXIN Injection and LANOXIN Injection Pediatric.

2.2 Loading Dosing Regimen in Adults and Pediatric Patients

Table 1. Recommended LANOXIN Injection Loading Dose
Age | Total IV Loading Dose (mcg/kg) Administer half the total loading dose initially, then ¼ the loading dose every 6-8 hours twice
Premature | 15-25
Full-Term | 20-30
1-24 Months | 30-50
2-5 Years | 25-35
5-10 Years | 15-30
Adults and pediatric patients over 10 years | 8-12
mcg = microgram

2.3 Maintenance Dosing in Adults and Pediatric Patients Over 10 Years Old

The maintenance dose is based on lean body weight, renal function, age, and concomitant products [see Clinical Pharmacology (12.3)] .

The recommended startingmaintenance doses in adults and pediatric patients over 10 years old with normal renal function are given in Table 2. Doses may be increased every 2 weeks according to clinical response, serum drug levels, and toxicity.

Table 2. Recommended Starting LANOXIN Injection Maintenance Dosage in Adults and Pediatric Patients Over 10 Years Old
Age | Total Intravenous Maintenance Dose, mcg/kg/day (given once daily)
Adults and pediatric patients over 10 years | 2.4-3.6
mcg = microgram

Table 3provides the recommended (once daily) maintenance dose for adults and pediatric patients over 10 years old (to be given once daily) according to lean body weight and renal function. The doses are based on studies in adult patients with heart failure. Alternatively, the maintenance dose may be estimated by the following formula (peak body stores lost each day through elimination):

Total Maintenance Dose = Loading Dose (i.e., Peak Body Stores) x % Daily Loss/100
(% Daily Loss = 14 + Creatinine clearance/5)

Reduce the dose of LANOXIN in patients whose lean weight is an abnormally small fraction of their total body mass because of obesity or edema.

Table 3. Recommended Maintenance Dose (in micrograms given once daily) of LANOXIN Injection in Pediatric Patients Over 10 Years Old and Adults by Lean Body Weight and by Renal Function
Corrected Creatinine Clearancea | Lean Body Weightc |  |  |  |  |  |  |  | Number of Days Before Steady State Achievedb
Corrected Creatinine Clearancea | kg | 40 | 50 | 60 | 70 | 80 | 90 | 100 | Number of Days Before Steady State Achievedb
Corrected Creatinine Clearancea |  |  |  |  |  |  |  |  | Number of Days Before Steady State Achievedb
10 mL/min |  | 64 | 80 | 96 | 112 | 128 | 144 | 160 | 19
20 mL/min |  | 72 | 90 | 108 | 126 | 144 | 162 | 180 | 16
30 mL/min |  | 80 | 100 | 120 | 140 | 160 | 180 | 200 | 14
40 mL/min |  | 88 | 110 | 132 | 154 | 176 | 198 | 220 | 13
50 mL/min |  | 96 | 120 | 144 | 168 | 192 | 216 | 240 | 12
60 mL/min |  | 104 | 130 | 156 | 182 | 208 | 234 | 260 | 11
70 mL/min |  | 112 | 140 | 168 | 196 | 224 | 252 | 280 | 10
80 mL/min |  | 120 | 150 | 180 | 210 | 240 | 270 | 300 | 9
90 mL/min |  | 128 | 160 | 192 | 224 | 256 | 288 | 320 | 8
100 mL/min |  | 136 | 170 | 204 | 238 | 272 | 306 | 340 | 7
a For adults, creatinine clearance was corrected to 70-kg body weight or 1.73 m^2body surface area. If only serum creatinine concentrations (Scr) are available, a corrected Ccr may be estimated in men as (140 – Age)/Scr. For women, this result should be multiplied by 0.85.
For pediatricpatients, the modified Schwartz equation may be used. The formula is based on height in cm and Scr in mg/dL where k is a constant. Ccr is corrected to 1.73 m^2body surface area. During the first year of life, the value of k is 0.33 for pre-term babies and 0.45 for term infants. The k is 0.55 for pediatric patients and adolescent girls and 0.7 for adolescent boys.
GFR (mL/min/1.73 m^2) = (k x Height)/Scr
b If no loading dose administered
c The doses listed assume average body composition.

2.4 Maintenance Dosing in Pediatric Patients Less Than 10 Years Old

The starting maintenance dose for heart failure in pediatric patients less than 10 years old is based on lean body weight, renal function, age, and concomitant products [see Clinical Pharmacology (12.3)] . The recommended startingmaintenance doses for pediatric patients are given in Table 4. These recommendations assume the presence of normal renal function.

Table 4. Recommended Starting LANOXIN Injection Maintenance Dosage in Pediatric Patients Less Than 10 Years Old
Age | Dose Regimen, mcg/kg/dose (given TWICE daily)
Premature | 1.9-3.1
Full-Term | 3-4.5
1-24 Months | 4.5-7.5
2-5 Years | 3.8-5.3
5-10 Years | 2.3-4.5
mcg = microgram

Table 5provides average daily maintenance dose requirements for pediatric patients less than 10 years old (to be given twice daily) with heart failure based on age, lean body weight, and renal function.

Table 5. Recommended Maintenance Dose (in micrograms given TWICE daily) of LANOXIN Injection in Pediatric Patients Less Than 10 Years of AgeaBased upon Lean Body Weight and Renal Functiona
Corrected Creatinine Clearanceb | Lean Body Weight |  |  |  |  |  |  |  | Number of Days Before Steady State Achievedc
Corrected Creatinine Clearanceb | kg | 5 | 10 | 20 | 30 | 40 | 50 | 60 | Number of Days Before Steady State Achievedc
Corrected Creatinine Clearanceb |  |  |  |  |  |  |  |  | Number of Days Before Steady State Achievedc
10 mL/min |  | 8 | 16 | 32 | 48 | 64 | 80 | 96 | 19
20 mL/min |  | 9 | 18 | 36 | 54 | 72 | 90 | 108 | 16
30 mL/min |  | 10 | 20 | 40 | 60 | 80 | 100 | 120 | 14
40 mL/min |  | 11 | 22 | 44 | 66 | 88 | 110 | 132 | 13
50 mL/min |  | 12 | 24 | 48 | 72 | 96 | 120 | 144 | 12
60 mL/min |  | 13 | 26 | 52 | 78 | 104 | 130 | 156 | 11
70 mL/min |  | 14 | 28 | 56 | 84 | 112 | 140 | 168 | 10
80 mL/min |  | 15 | 30 | 60 | 90 | 120 | 150 | 180 | 9
90 mL/min |  | 16 | 32 | 64 | 96 | 128 | 160 | 192 | 8
100 mL/min |  | 17 | 34 | 68 | 102 | 136 | 170 | 204 | 7
a Recommended are doses to be given twice daily.
b The modified Schwartz equation may be used to estimate creatinine clearance. See footnote a under Table 3.
c If no loading dose administered.

2.5 Monitoring to Assess Safety, Efficacy, and Therapeutic Blood Levels

Monitor for signs and symptoms of digoxin toxicity and clinical response. Adjust dose based on toxicity, efficacy, and blood levels.

Serum digoxin levels less than 0.5 ng/mL have been associated with diminished efficacy, while levels above 2 ng/mL have been associated with increased toxicity without increased benefit.

Interpret the serum digoxin concentration in the overall clinical context, and do not use an isolated measurement of serum digoxin concentration as the basis for increasing or decreasing the LANOXIN dose. Serum digoxin concentrations may be falsely elevated by endogenous digoxin-like substances [see Drug Interactions (7.4)] . If the assay is sensitive to these substances, consider obtaining a baseline digoxin level before starting LANOXIN and correct post-treatment values by the reported baseline level.

Obtain serum digoxin concentrations just before the next scheduled LANOXIN dose or at least 6 hours after the last dose. The digoxin concentration is likely to be 10-25% lower when sampled right before the next dose (24 hours after dosing) compared to sampling 8 hours after dosing (using once-daily dosing). However, there will be only minor differences in digoxin concentrations using twice daily dosing whether sampling is done at 8 or 12 hours after a dose.

2.6 Switching from Intravenous Digoxin to Oral Digoxin

When switching from intravenous to oral digoxin formulations, make allowances for differences in bioavailability when calculating maintenance dosages (see Table 6).

Table 6. Comparison of the Systemic Availability and Equivalent Doses of Oral and Intravenous LANOXIN
 | Absolute Bioavailability | Equivalent Doses (mcg)
LANOXIN Tablets | 60-80% | 62.5 | 125 | 250 | 500
LANOXIN Intravenous Injection | 100% | 50 | 100 | 200 | 400

3 DOSAGE FORMS AND STRENGTHS

LANOXIN Injection: 500 mcg/2 mL (250 mcg/mL) single-dose ampule.
LANOXIN Injection: 500 mcg/2 mL (250 mcg/ mL) single-dose vial.

LANOXIN Injection Pediatric: 100 mcg/mL single-dose ampule.
LANOXIN Injection Pediatric: 100 mcg/mL single-dose vial.

4 CONTRAINDICATIONS

LANOXIN is contraindicated in patients with:

- Ventricular fibrillation [see Warnings and Precautions (5.1)]
- Known hypersensitivity to digoxin (reactions seen include unexplained rash, swelling of the mouth, lips or throat or a difficulty in breathing). A hypersensitivity reaction to other digitalis preparations usually constitutes a contraindication to digoxin.

5 WARNINGS AND PRECAUTIONS

5.1 Ventricular Fibrillation in Patients With Accessory AV Pathway (Wolff-Parkinson-White Syndrome)

Patients with Wolff-Parkinson-White syndrome who develop atrial fibrillation are at high risk of ventricular fibrillation. Treatment of these patients with digoxin leads to greater slowing of conduction in the atrioventricular node than in accessory pathways, and the risks of rapid ventricular response leading to ventricular fibrillation are thereby increased.

5.2 Sinus Bradycardia and Sino-atrial Block

LANOXIN may cause severe sinus bradycardia or sinoatrial block particularly in patients with pre-existing sinus node disease and may cause advanced or complete heart block in patients with pre-existing incomplete AV block. Consider insertion of a pacemaker before treatment with digoxin.

5.3 Digoxin Toxicity

Signs and symptoms of digoxin toxicity include anorexia, nausea, vomiting, visual changes and cardiac arrhythmias [first-degree, second-degree (Wenckebach), or third-degree heart block (including asystole); atrial tachycardia with block; AV dissociation; accelerated junctional (nodal) rhythm; unifocal or multiform ventricular premature contractions (especially bigeminy or trigeminy); ventricular tachycardia; and ventricular fibrillation]. Toxicity is usually associated with digoxin levels greater than 2 ng/mL although symptoms may also occur at lower levels. Low body weight, advanced age or impaired renal function, hypokalemia, hypercalcemia, or hypomagnesemia may predispose to digoxin toxicity. Obtain serum digoxin levels in patients with signs or symptoms of digoxin therapy and interrupt or adjust dose if necessary [see Adverse Reactions (6) and Overdosage (10)]. Assess serum electrolytes and renal function periodically.

The earliest and most frequent manifestation of digoxin toxicity in infants and children is the appearance of cardiac arrhythmias, including sinus bradycardia. In children, the use of digoxin may produce any arrhythmia. The most common are conduction disturbances or supraventricular tachyarrhythmias, such as atrial tachycardia (with or without block) and junctional (nodal) tachycardia. Ventricular arrhythmias are less common. Sinus bradycardia may be a sign of impending digoxin intoxication, especially in infants, even in the absence of first-degree heart block. Any arrhythmias or alteration in cardiac conduction that develops in a child taking digoxin should initially be assumed to be a consequence of digoxin intoxication.

Given that adult patients with heart failure have some symptoms in common with digoxin toxicity, it may be difficult to distinguish digoxin toxicity from heart failure. Misidentification of their etiology might lead the clinician to continue or increase LANOXIN dosing, when dosing should actually be suspended. When the etiology of these signs and symptoms is not clear, measure serum digoxin levels.

5.4 Risk of Ventricular Arrhythmias During Electrical Cardioversion

It may be desirable to reduce the dose of or discontinue LANOXIN for 1-2 days prior to electrical cardioversion of atrial fibrillation to avoid the induction of ventricular arrhythmias, but physicians must consider the consequences of increasing the ventricular response if digoxin is decreased or withdrawn. If digitalis toxicity is suspected, elective cardioversion should be delayed. If it is not prudent to delay cardioversion, the lowest possible energy level should be selected to avoid provoking ventricular arrhythmias.

5.5 Risk of Ischemia in Patients With Acute Myocardial Infarction

LANOXIN is not recommended in patients with acute myocardial infarction because digoxin may increase myocardial oxygen demand and lead to ischemia.

5.6 Vasoconstriction In Patients With Myocarditis

LANOXIN can precipitate vasoconstriction and may promote production of pro-inflammatory cytokines; therefore, avoid use in patients with myocarditis.

5.7 Decreased Cardiac Output in Patients With Preserved Left Ventricular Systolic Function

Patients with heart failure associated with preserved left ventricular ejection fraction may experience decreased cardiac output with use of LANOXIN. Such disorders include restrictive cardiomyopathy, constrictive pericarditis, amyloid heart disease, and acute cor pulmonale. Patients with idiopathic hypertrophic subaortic stenosis may have worsening of the outflow obstruction due to the inotropic effects of digoxin. Patients with amyloid heart disease may be more susceptible to digoxin toxicity at therapeutic levels because of an increased binding of digoxin to extracellular amyloid fibrils.

LANOXIN should generally be avoided in these patients, although it has been used for ventricular rate control in the subgroup of patients with atrial fibrillation.

5.8 Reduced Efficacy In Patients With Hypocalcemia

Hypocalcemia can nullify the effects of digoxin in humans; thus, digoxin may be ineffective until serum calcium is restored to normal. These interactions are related to the fact that digoxin affects contractility and excitability of the heart in a manner similar to that of calcium.

5.9 Altered Response in Thyroid Disorders and Hypermetabolic States

Hypothyroidism may reduce the requirements for digoxin.

Heart failure and/or atrial arrhythmias resulting from hypermetabolic or hyperdynamic states (e.g., hyperthyroidism, hypoxia, or arteriovenous shunt) are best treated by addressing the underlying condition. Atrial arrhythmias associated with hypermetabolic states are particularly resistant to digoxin treatment. Patients with beri beri heart disease may fail to respond adequately to digoxin if the underlying thiamine deficiency is not treated concomitantly.

6 ADVERSE REACTIONS

The following adverse reactions are included in more detail in the Warnings and Precautions section of the label:

- Cardiac arrhythmias [see Warnings and Precautions (5.1, 5.2)]
- Digoxin Toxicity [see Warnings and Precautions (5.3)]

6.1 Clinical Trials Experience

Because clinical trials are conducted under widely varying conditions, adverse reaction rates observed in the clinical trials of a drug cannot be directly compared to rates in the clinical trials of another drug and may not reflect the rates observed in clinical practice.

In general, the adverse reactions of LANOXIN are dose-dependent and occur at doses higher than those needed to achieve a therapeutic effect. Hence, adverse reactions are less common when LANOXIN is used within the recommended dose range, is maintained within the therapeutic serum concentration range, and when there is careful attention to concurrent medications and conditions.

In the DIG trial (a trial investigating the effect of digoxin on mortality and morbidity in patients with heart failure), the incidence of hospitalization for suspected digoxin toxicity was 2% in patients taking LANOXIN compared to 0.9% in patients taking placebo [see Clinical Studies (14.1)] .

The overall incidence of adverse reactions with digoxin has been reported as 5-20%, with 15-20% of adverse events considered serious. Cardiac toxicity accounts for about one-half, gastrointestinal disturbances for about one-fourth, and CNS and other toxicity for about one-fourth of these adverse events.

Gastrointestinal:In addition to nausea and vomiting, the use of digoxin has been associated with abdominal pain, intestinal ischemia, and hemorrhagic necrosis of the intestines.

CNS: Digoxin can cause headache, weakness, dizziness, apathy, confusion, and mental disturbances (such as anxiety, depression, delirium, and hallucination).

Other:Gynecomastia has been occasionally observed following the prolonged use of digoxin. Thrombocytopenia and maculopapular rash and other skin reactions have been rarely observed.

7 DRUG INTERACTIONS

Digoxin has a narrow therapeutic index, increased monitoring of serum digoxin concentrations and for potential signs and symptoms of clinical toxicity is necessary when initiating, adjusting, or discontinuing drugs that may interact with digoxin. Prescribers should consult the prescribing information of any drug which is co-prescribed with digoxin for potential drug interaction information.

7.1 P-Glycoprotein (PGP) Inducers/Inhibitors

Digoxin is a substrate of P-glycoprotein, at the level of intestinal absorption, renal tubular section and biliary-intestinal secretion. Therefore, drugs that induce/ inhibit P-glycoprotein have the potential to alter digoxin pharmacokinetics.

7.2 Pharmacokinetic Drug Interactions

Pharmacokinetic interactions have been observed and reported primarily when digoxin is co-administered by oral route. There are very few studies that have evaluated the drug interaction when digoxin is administered via IV route. The magnitude of digoxin exposure change through IV route is generally lower than that through oral route. Table below provides available interaction data using digoxin IV formulation (NA means not available).

Digoxin concentrations increased greater than 50%
 | Digoxin Serum Concentration Increase | Digoxin AUC Increase | Recommendations
Quinidine | NA | 54-83% | Measure serum digoxin concentrations before initiating concomitant drugs. Reduce digoxin concentrations by decreasing dose by approximately 30-50% or by modifying the dosing frequency and continue monitoring.
Ritonavir | NA | 86% | Measure serum digoxin concentrations before initiating concomitant drugs. Reduce digoxin concentrations by decreasing dose by approximately 30-50% or by modifying the dosing frequency and continue monitoring.
Digoxin concentrations increased less than 50%
Amiodarone | 17% | 40% | Measure serum digoxin concentrations before initiating concomitant drugs. Reduce digoxin concentrations by decreasing the dose by approximately 15-30% or by modifying the dosing frequency and continue monitoring.
Propafenone | 28% | 29% | Measure serum digoxin concentrations before initiating concomitant drugs. Reduce digoxin concentrations by decreasing the dose by approximately 15-30% or by modifying the dosing frequency and continue monitoring.
Quinine | NA | 34-38% | Measure serum digoxin concentrations before initiating concomitant drugs. Reduce digoxin concentrations by decreasing the dose by approximately 15-30% or by modifying the dosing frequency and continue monitoring.
Spironolactone | NA | 44% | Measure serum digoxin concentrations before initiating concomitant drugs. Reduce digoxin concentrations by decreasing the dose by approximately 15-30% or by modifying the dosing frequency and continue monitoring.
Verapamil | NA | 24% | Measure serum digoxin concentrations before initiating concomitant drugs. Reduce digoxin concentrations by decreasing the dose by approximately 15-30% or by modifying the dosing frequency and continue monitoring.
Mirabegron | 29% | 27%

7.3 Potentially Significant Pharmacodynamic Drug Interactions

Because of considerable variability of pharmacodynamic interactions, the dosage of digoxin should be individualized when patients receive these medications concurrently.

Drugs that Affect Renal Function | A decline in GFR or tubular secretion, as from ACE inhibitors, angiotensin receptor blockers, nonsteroidal anti-inflammatory drugs [NSAIDs], COX-2 inhibitors may impair the excretion of digoxin.
Antiarrthymics | Dofetilide | Concomitant administration with digoxin was associated with a higher rate of torsades de pointes.
 | Sotalol | Proarrhythmic events were more common in patients receiving sotalol and digoxin than on either alone; it is not clear whether this represents an interaction or is related to the presence of CHF, a known risk factor for proarrhythmia, in patients receiving digoxin.
 | Dronedarone | Sudden death was more common in patients receiving digoxin with dronedarone than on either alone; it is not clear whether this represents an interaction or is related to the presence of advanced heart disease, a known risk factor for sudden death in patients receiving digoxin.
Parathyroid Hormone Analog | Teriparatide | Sporadic case reports have suggested that hypercalcemia may predispose patients to digitalis toxicity. Teriparatide transiently increases serum calcium.
Thyroid supplement | Thyroid | Treatment of hypothyroidism in patients taking digoxin may increase the dose requirements of digoxin.
Sympathomimetics | Epinephrine Norepinephrine Dopamine | Can increase the risk of cardiac arrhythmias.
Neuromuscular Blocking Agents | Succinylcholine | May cause sudden extrusion of potassium from muscle cells, causing arrhythmias in patients taking digoxin.
Supplements | Calcium | If administered rapidly by intravenous route, can produce serious arrhythmias in digitalized patients.
Beta-adrenergic blockers and calcium channel blockers |  | Additive effects on AV node conduction can result in bradycardia and advanced or complete heart block.
Ivabradine | Can increase the risk of bradycardia.

7.4 Drug/Laboratory Test Interactions

Endogenous substances of unknown composition (digoxin-like immunoreactive substances [DLIS]) can interfere with standard radioimmunoassays for digoxin. The interference most often causes results to be falsely positive or falsely elevated, but sometimes it causes results to be falsely reduced. Some assays are more subject to these failings than others. Several LC/MS/MS methods are available that may provide less susceptibility to DLIS interference. DLIS are present in up to half of all neonates and in varying percentages of pregnant women, patients with hypertrophic cardiomyopathy, patients with renal or hepatic dysfunction, and other patients who are volume-expanded for any reason. The measured levels of DLIS (as digoxin equivalents) are usually low (0.2-0.4 ng/mL), but sometimes they reach levels that would be considered therapeutic or even toxic.

In some assays, spironolactone, canrenone, and potassium canrenoate may be falsely detected as digoxin, at levels up to 0.5 ng/mL. Some traditional Chinese and Ayurvedic medicine substances like Chan Su, Siberian Ginseng, Asian Ginseng, Ashwagandha, or Danshen can cause similar interference.

Spironolactone and DLIS are much more extensively protein-bound than digoxin. As a result, assays of free digoxin levels in protein-free ultrafiltrate (which tend to be about 25% less than total levels, consistent with the usual extent of protein binding) are less affected by spironolactone or DLIS. It should be noted that ultrafiltration does not solve all interference problems with alternative medicines. The use of an LC/MS/MS method may be the better option according to the good results it provides, especially in terms of specificity and limit of quantization.

8 USE IN SPECIFIC POPULATIONS

8.1 Pregnancy

Risk Summary

Experience with digoxin in pregnant women over several decades, based on published retrospective clinical studies and case reports, has not led to the identification of a drug associated risk of major birth defects, miscarriage or adverse maternal and fetal outcomes. Untreated underlying maternal conditions, such as heart failure and atrial fibrillation, during pregnancy pose a risk to the mother and fetus (see Clinical Consideration). Animal reproduction studies have not been conducted with digoxin.

The estimated background risk of major birth defects and miscarriage for the indicated population(s) are unknown. All pregnancies have a background risk of birth defect, loss, or other adverse outcomes. In the U.S. general population, the estimated background risk of major birth defects and miscarriage in clinically recognized pregnancies is 2-4% and 15-20%, respectively.

Clinical Considerations

Disease-associated maternal and/or embryo/fetal risk

Pregnant women with heart failure are at increased risk for preterm birth. Clinical classification of heart disease may worsen with pregnancy and lead to maternal or fetal death.

Pregnant women with atrial fibrillation are at an increased risk of delivering a low birth weight infant. Atrial fibrillation may worsen with pregnancy and can lead to maternal or fetal death.

Fetal/neonatal adverse reactions

Digoxin has been shown to cross the placenta and is found in amniotic fluid. Monitor neonates for signs and symptoms of digoxin toxicity, including vomiting, and cardiac arrhythmias [see Warnings and Precautions (5.3)].

Dose adjustments during pregnancy and the postpartum period

LANOXIN requirements may increase during pregnancy and decrease in the postpartum period. Monitor serum digoxin levels during pregnancy and the postpartum period [see Dosage and Administration (2.5)].

Labor or Delivery

Risk of arrhythmias may increase during the labor and delivery. Monitor patients continuously during labor and delivery [see Warnings and Precautions (5.1 and 5.2)].

8.2 Lactation

Risk Summary

The digoxin dose received through breastfeeding is up to 4% of the neonatal maintenance dosage, which is unlikely to be clinically relevant. There are no data on the effects of digoxin on the breastfed infant or the effects on milk production.

Data

Based on data from two lactation studies in a total of 13 breastfed infants, the digoxin concentrations in breast milk were between 0.4 – 1.0 ng/mL following 0.25 mg once daily dose of digoxin in the lactating mother. Thus, the amount of digoxin ingested daily by the infants is estimated to be between 0.03 to 0.16 mcg/kg/day. This translates to a relative infant dose of digoxin between 1 to 7% of the maternal weight-adjusted dose and about 0.2 to 4% of the neonatal maintenance dose.

8.4 Pediatric Use

The safety and effectiveness of LANOXIN in the control of ventricular rate in children with atrial fibrillation have not been established.

The safety and effectiveness of LANOXIN in the treatment of heart failure in children have not been established in adequate and well-controlled studies. However, in published literature of children with heart failure of various etiologies (e.g., ventricular septal defects, anthracycline toxicity, patent ductus arteriosus), treatment with digoxin has been associated with improvements in hemodynamic parameters and in clinical signs and symptoms.

Newborn infants display considerable variability in their tolerance to digoxin. Premature and immature infants are particularly sensitive to the effects of digoxin, and the dosage of the drug must not only be reduced but must be individualized according to their degree of maturity.

8.5 Geriatric Use

The majority of clinical experience gained with digoxin has been in the elderly population. This experience has not identified differences in response or adverse effects between the elderly and younger patients. However, this drug is known to be substantially excreted by the kidney, and the risk of toxic reactions to this drug may be greater in patients with impaired renal function. Because elderly patients are more likely to have decreased renal function, care should be taken in dose selection, which should be based on renal function, and it may be useful to monitor renal function [see Dosage and Administration (2.1)] .

8.6 Renal Impairment

The clearance of digoxin can be primarily correlated with the renal function as indicated by creatinine clearance. Table 3and Table 5provide the usual daily maintenance dose requirements for digoxin based on creatinine clearance [see Dosage and Administration (2.3)] .

Digoxin is primarily excreted by the kidneys; therefore, patients with impaired renal function require smaller than usual maintenance doses of digoxin [see Dosage and Administration (2.3)] . Because of the prolonged elimination half-life, a longer period of time is required to achieve an initial or new steady-state serum concentration in patients with renal impairment than in patients with normal renal function. If appropriate care is not taken to reduce the dose of digoxin, such patients are at high risk for toxicity, and toxic effects will last longer in such patients than in patients with normal renal function.

8.7 Hepatic Impairment

Plasma digoxin concentrations in patients with acute hepatitis generally fall within the range of profiles in a group of healthy subjects.

8.8 Malabsorption

The absorption of digoxin is reduced in some malabsorption conditions such as chronic diarrhea.

10 OVERDOSAGE

10.1 Signs and Symptoms in Adults and Children

The signs and symptoms of toxicity are generally similar to those previously described [see Adverse Reactions (6.1)] but may be more frequent and can be more severe. Signs and symptoms of digoxin toxicity become more frequent with levels above 2 ng/mL. However, in deciding whether a patient’s symptoms are due to digoxin, the clinical state together with serum electrolyte levels and thyroid function are important factors [see Dosage and Administration (2)] .

Adults:The most common signs and symptoms of digoxin toxicity are nausea, vomiting, anorexia, and fatigue that occur in 30-70% of patients who are overdosed. Extremely high serum concentrations produce hyperkalemia especially in patients with impaired renal function. Almost every type of cardiac arrhythmia has been associated with digoxin overdose and multiple rhythm disturbances in the same patient are common. Peak cardiac effects occur 3-6 hours following ingestion and may persist for 24 hours or longer. Arrhythmias that are considered more characteristic of digoxin toxicity are new-onset Mobitz type 1 A-V block, accelerated junctional rhythms, non-paroxysmal atrial tachycardia with A-V block, and bi-directional ventricular tachycardia. Cardiac arrest from asystole or ventricular fibrillation is usually fatal.

Digoxin toxicity is related to serum concentration. As digoxin serum levels increase above 1.2 ng/mL, there is a potential for increase in adverse reactions. Furthermore, lower potassium levels increases the risk for adverse reactions. In adults with heart disease, clinical observations suggest that an overdose of digoxin of 10-15 mg results in death of half of patients. A dose above 25 mg ingested by an adult without heart disease appeared to be uniformly fatal if no Digoxin Immune Fab (DIGIBIND®, DIGIFAB®) was administered.

Among the extra-cardiac manifestations, gastrointestinal symptoms (e.g., nausea, vomiting, anorexia) are very common (up to 80% incidence) and precede cardiac manifestations in approximately half of the patients in most literature reports. Neurologic manifestations (e.g., dizziness, various CNS disturbances), fatigue, and malaise are very common. Visual manifestations may also occur with aberration in color vision (predominance of yellow green) the most frequent. Neurological and visual symptoms may persist after other signs of toxicity have resolved. In chronic toxicity, nonspecific extra-cardiac symptoms, such as malaise and weakness, may predominate.

Children:In pediatric patients, signs and symptoms of toxicity can occur during or shortly after the dose of digoxin. Frequent non-cardiac effects are similar to those observed in adults although nausea and vomiting are not seen frequently in infants and small pediatric patients. Other reported manifestations of overdose are weight loss in older age groups, failure to thrive in infants, abdominal pain caused by mesenteric artery ischemia, drowsiness, and behavioral disturbances including psychotic episodes. Arrhythmias and combinations of arrhythmias that occur in adult patients can also occur in pediatric patients although sinus tachycardia, supraventricular tachycardia, and rapid atrial fibrillation are seen less frequently in pediatric patients. Pediatric patients are more likely to develop A-V conduction disturbances, or sinus bradycardia. Any arrhythmia in a child treated with digoxin should be considered related to digoxin until otherwise ruled out. In pediatric patients aged 1-3 years without heart disease, clinical observations suggest that an overdose of digoxin of 6-10 mg would result in death of half of the patients. In the same population, a dose above 10 mg resulted in death if no Digoxin Immune Fab were administered.

10.2 Treatment

Chronic Overdose

If there is suspicion of toxicity, discontinue LANOXIN and place the patient on a cardiac monitor. Correct factors such as electrolyte abnormalities, thyroid dysfunction, and concomitant medications [see Dosage and Administration (2.5)]. Correct hypokalemia by administering potassium so that serum potassium is maintained between 4 and 5.5 mmol/L. Potassium is usually administered orally, but when correction of the arrhythmia is urgent and serum potassium concentration is low, potassium may be administered by the intravenous route. Monitor electrocardiogram for any evidence of potassium toxicity (e.g., peaking of T waves) and to observe the effect on the arrhythmia. Avoid potassium salts in patients with bradycardia or heart block. Symptomatic arrhythmias may be treated with Digoxin Immune Fab.

Acute Overdose

Patients who have intentionally or accidently ingested massive doses of digoxin should receive activated charcoal orally or by nasogastric tube regardless of the time since ingestion since digoxin recirculates to the intestine by enterohepatic circulation. In addition to cardiac monitoring, temporarily discontinue LANOXIN until the adverse reaction resolves. Correct factors that may be contributing to the adverse reactions [see Warnings and Precautions (5)] . In particular, correct hypokalemia and hypomagnesemia. Digoxin is not effectively removed from the body by dialysis because of its large extravascular volume of distribution. Life threatening arrhythmias (ventricular tachycardia, ventricular fibrillation, high degree A-V block, bradyarrhythma, sinus arrest) or hyperkalemia requires administration of Digoxin Immune Fab. Digoxin Immune Fab has been shown to be 80-90% effective in reversing signs and symptoms of digoxin toxicity. Bradycardia and heart block caused by digoxin are parasympathetically mediated and respond to atropine. A temporary cardiac pacemaker may also be used. Ventricular arrhythmias may respond to lidocaine or phenytoin. When a large amount of digoxin has been ingested, especially in patients with impaired renal function, hyperkalemia may be present due to release of potassium from skeletal muscle. In this case, treatment with Digoxin Immune Fab is indicated; an initial treatment with glucose and insulin may be needed if the hyperkalemia is life-threatening. Once the adverse reaction has resolved, therapy with LANOXIN may be reinstituted following a careful reassessment of dose.

11 DESCRIPTION

LANOXIN (digoxin) is one of the cardiac (or digitalis) glycosides, a closely related group of drugs having in common specific effects on the myocardium. These drugs are found in a number of plants. Digoxin is extracted from the leaves of Digitalis lanata. The term “digitalis” is used to designate the whole group of glycosides. The glycosides are composed of 2 portions: a sugar and a cardenolide (hence “glycosides”).

Digoxin is described chemically as (3β,5β,12β)-3-[(O-2,6-dideoxy-β- D-ribo-hexopyranosyl-(1→4)- O-2,6-dideoxy-β- D-ribo-hexopyranosyl-(1→4)-2,6-dideoxy-β- D-ribo-hexopyranosyl)oxy]-12,14-dihydroxy-card-20(22)-enolide. Its molecular formula is C41H64O14, its molecular weight is 780.95, and its structural formula is:

Digoxin exists as odorless white crystals that melt with decomposition above 230°C. The drug is practically insoluble in water and in ether; slightly soluble in diluted (50%) alcohol and in chloroform; and freely soluble in pyridine.

LANOXIN Injection and Injection Pediatric are sterile solutions of digoxin for intravenous or intramuscular injection. The vehicle contains 42.5% (W/V) propylene glycol and 10% alcohol (V/V). The injection is buffered to a pH of 6.8-7.2 with 0.17% dibasic sodium phosphate and 0.08% anhydrous citric acid. Each 2-mL single-dose ampule or vial of LANOXIN Injection contains 500 mcg digoxin (250 mcg/mL). Dilution is not required. Each 1-mL single-dose ampule or vial of LANOXIN Injection Pediatric contains 100 mcg digoxin (100 mcg/mL). Dilution is not required.

12 CLINICAL PHARMACOLOGY

12.1 Mechanism of Action

All of digoxin’s actions are mediated through its effects on Na-K ATPase. This enzyme, the “sodium pump,” is responsible for maintaining the intracellular milieu throughout the body by moving sodium ions out of and potassium ions into cells. By inhibiting Na-K ATPase, digoxin

- causes increased availability of intracellular calcium in the myocardium and conduction system, with consequent increased inotropy, increased automaticity, and reduced conduction velocity
- indirectly causes parasympathetic stimulation of the autonomic nervous system, with consequent effects on the sino-atrial (SA) and atrioventricular (AV) nodes
- reduces catecholamine reuptake at nerve terminals, rendering blood vessels more sensitive to endogenous or exogenous catecholamines
- increases baroreceptor sensitization, with consequent increased carotid sinus nerve activity and enhanced sympathetic withdrawal for any given increment in mean arterial pressure
- increases (at higher concentrations) sympathetic outflow from the central nervous system (CNS) to both cardiac and peripheral sympathetic nerves
- allows (at higher concentrations) progressive efflux of intracellular potassium, with consequent increase in serum potassium levels.

The cardiologic consequences of these direct and indirect effects are an increase in the force and velocity of myocardial systolic contraction (positive inotropic action), a slowing of the heart rate (negative chronotropic effect), decreased conduction velocity through the AV node, and a decrease in the degree of activation of the sympathetic nervous system and renin-angiotensin system (neurohormonal deactivating effect).

12.2 Pharmacodynamics

The times to onset of pharmacologic effect and to peak effect of preparations of LANOXIN are shown in Table 7.

Table 7. Times to Onset of Pharmacologic Effect and to Peak Effect of Preparations of LANOXIN
Product | Time to Onset of Effecta | Time to Peak Effecta
LANOXIN Tablets | 0.5-2 hours | 2-6 hours
LANOXIN Injection/IV | 5-30 minutesb | 1-4 hours
a Documented for ventricular response rate in atrial fibrillation, inotropic effects and electrocardiographic changes.
b Depending upon rate of infusion.

Hemodynamic Effects:Short- and long-term therapy with the drug increases cardiac output and lowers pulmonary artery pressure, pulmonary capillary wedge pressure, and systemic vascular resistance in patients with heart failure. These hemodynamic effects are accompanied by an increase in the left ventricular ejection fraction and a decrease in end-systolic and end-diastolic dimensions.

ECG Changes:The use of therapeutic doses of LANOXIN may cause prolongation of the PR interval and depression of the ST segment on the electrocardiogram. LANOXIN may produce false positive ST-T changes on the electrocardiogram during exercise testing. These electrophysiologic effects are not indicative of toxicity. LANOXIN does not significantly reduce heart rate during exercise.

12.3 Pharmacokinetics

Note: The following data are from studies performed in adults, unless otherwise stated.

Comparisons of the systemic availability and equivalent doses for oral preparations of LANOXIN are shown in Table 6 [see Dosage and Administration (2.6)] .

Distribution:Following drug administration, a 6-8 hour tissue distribution phase is observed. This is followed by a much more gradual decline in the serum concentration of the drug, which is dependent on the elimination of digoxin from the body. The peak height and slope of the early portion (absorption/distribution phases) of the serum concentration-time curve are dependent upon the route of administration and the absorption characteristics of the formulation. Clinical evidence indicates that the early high serum concentrations do not reflect the concentration of digoxin at its site of action, but that with chronic use, the steady-state post-distribution serum concentrations are in equilibrium with tissue concentrations and correlate with pharmacologic effects. In individual patients, these post-distribution serum concentrations may be useful in evaluating therapeutic and toxic effects [see Dosage and Administration (2.1)] .

Digoxin is concentrated in tissues and therefore has a large apparent volume of distribution (approximately 475-500 L). Digoxin crosses both the blood-brain barrier and the placenta. At delivery, the serum digoxin concentration in the newborn is similar to the serum concentration in the mother. Approximately 25% of digoxin in the plasma is bound to protein. Serum digoxin concentrations are not significantly altered by large changes in fat tissue weight, so that its distribution space correlates best with lean (i.e., ideal) body weight, not total body weight.

Metabolism:Only a small percentage (13%) of a dose of digoxin is metabolized in healthy volunteers. The urinary metabolites, which include dihydrodigoxin, digoxigenin bisdigitoxoside, and their glucuronide and sulfate conjugates are polar in nature and are postulated to be formed via hydrolysis, oxidation, and conjugation. The metabolism of digoxin is not dependent upon the cytochrome P-450 system, and digoxin is not known to induce or inhibit the cytochrome P-450 system.

Excretion:Elimination of digoxin follows first-order kinetics (that is, the quantity of digoxin eliminated at any time is proportional to the total body content). Following intravenous administration to healthy volunteers, 50-70% of a digoxin dose is excreted unchanged in the urine. Renal excretion of digoxin is proportional to creatinine clearance and is largely independent of urine flow. In healthy volunteers with normal renal function, digoxin has a half-life of 1.5-2 days. The half-life in anuric patients is prolonged to 3.5-5 days. Digoxin is not effectively removed from the body by dialysis, exchange transfusion, or during cardiopulmonary bypass because most of the drug is bound to extravascular tissues.

Special Populations: Geriatrics:Because of age-related declines in renal function, elderly patients would be expected to eliminate digoxin more slowly than younger subjects. Elderly patients may also exhibit a lower volume of distribution of digoxin due to age-related loss of lean muscle mass. Thus, the dosage of digoxin should be carefully selected and monitored in elderly patients [see Use in Specific Populations (8.5)] .

Gender:In a study of 184 patients, the clearance of digoxin was 12% lower in female than in male patients. This difference is not likely to be clinically important.

Hepatic Impairment:Because only a small percentage (approximately 13%) of a dose of digoxin undergoes metabolism, hepatic impairment would not be expected to significantly alter the pharmacokinetics of digoxin. In a small study, plasma digoxin concentration profiles in patients with acute hepatitis generally fell within the range of profiles in a group of healthy subjects. No dosage adjustments are recommended for patients with hepatic impairment; however, serum digoxin concentrations should be used, as appropriate, to help guide dosing in these patients.

Renal Impairment:Since the clearance of digoxin correlates with creatinine clearance, patients with renal impairment generally demonstrate prolonged digoxin elimination half-lives and greater exposures to digoxin. Therefore, titrate carefully in these patients based on clinical response and based on monitoring of serum digoxin concentrations, as appropriate.

Race:The impact of race differences on digoxin pharmacokinetics has not been formally studied. Because digoxin is primarily eliminated as unchanged drug via the kidney and because there are no important differences in creatinine clearance among races, pharmacokinetic differences due to race are not expected.

13 NONCLINICAL TOXICOLOGY

13.1 Carcinogenesis, Mutagenesis, Impairment of Fertility

Digoxin showed no genotoxic potential in in vitrostudies (Ames test and mouse lymphoma). No data are available on the carcinogenic potential of digoxin, nor have studies been conducted to assess its potential to affect fertility.

14 CLINICAL STUDIES

14.1 Chronic Heart Failure

Two 12-week, double-blind, placebo-controlled studies enrolled 178 (RADIANCE trial) and 88 (PROVED trial) adult patients with NYHA Class II or III heart failure previously treated with oral digoxin, a diuretic, and an ACE inhibitor (RADIANCE only) and randomized them to placebo or treatment with LANOXIN Tablets. Both trials demonstrated better preservation of exercise capacity in patients randomized to LANOXIN. Continued treatment with LANOXIN reduced the risk of developing worsening heart failure, as evidenced by heart failure-related hospitalizations and emergency care and the need for concomitant heart failure therapy.

DIG Trial of LANOXIN in Patients with Heart Failure

The Digitalis Investigation Group (DIG) main trial was a 37-week, multicenter, randomized, double-blind mortality study comparing digoxin to placebo in 6800 adult patients with heart failure and left ventricular ejection fraction less than or equal to 0.45. At randomization, 67% were NYHA class I or II, 71% had heart failure of ischemic etiology, 44% had been receiving digoxin, and most were receiving a concomitant ACE inhibitor (94%) and diuretics (82%). As in the smaller trials described above, patients who had been receiving open-label digoxin were withdrawn from this treatment before randomization. Randomization to digoxin was again associated with a significant reduction in the incidence of hospitalization, whether scored as number of hospitalizations for heart failure (relative risk 75%), risk of having at least one such hospitalization during the trial (RR 72%), or number of hospitalizations for any cause (RR 94%). On the other hand, randomization to digoxin had no apparent effect on mortality (RR 99%, with confidence limits of 91-107%).

14.2 Chronic Atrial Fibrillation

Digoxin has also been studied as a means of controlling the ventricular response to chronic atrial fibrillation in adults. Digoxin reduced the resting heart rate, but not the heart rate during exercise.

In 3 different randomized, double-blind trials that included a total of 315 adult patients, digoxin was compared to placebo for the conversion of recent-onset atrial fibrillation to sinus rhythm. Conversion was equally likely, and equally rapid, in the digoxin and placebo groups. In a randomized 120-patient trial comparing digoxin, sotalol, and amiodarone, patients randomized to digoxin had the lowest incidence of conversion to sinus rhythm, and the least satisfactory rate control when conversion did not occur.

In at least one study, digoxin was studied as a means of delaying reversion to atrial fibrillation in adult patients with frequent recurrence of this arrhythmia. This was a randomized, double-blind, 43-patient crossover study. Digoxin increased the mean time between symptomatic recurrent episodes by 54%, but had no effect on the frequency of fibrillatory episodes seen during continuous electrocardiographic monitoring.

16 HOW SUPPLIED/STORAGE AND HANDLING

LANOXIN (digoxin) Injection, 500 mcg/2 mL (250 mcg/mL); box of 10 single-dose ampules (NDC 70515 260 10)

LANOXIN (digoxin) Injection, 500 mcg/2 mL (250 mcg/mL); box of 10 single-dose vials (NDC 70515 261 10)

LANOXIN (digoxin) Injection Pediatric, 100 mcg/mL; box of 10 single-dose ampules (NDC 70515 262 10)

LANOXIN (digoxin) Injection Pediatric, 100 mcg/mL; box of 10 single-dose vials (NDC 70515 263 10)

Store at 25 °C (77 °F); excursions permitted to 15 °C to 30 °C (59 °F to 86 °F) [see USP Controlled Room Temperature] and protect from light. Discard unused portion.

17 PATIENT COUNSELING INFORMATION

•Advise patients to contact their doctor or a health care professional if they experience nausea, vomiting, persistent diarrhea, confusion, weakness, or visual disturbances (including blurred vision, green-yellow color disturbances, halo effect) as these could be signs that the dose of LANOXIN may be too high.•Advise parents or caregivers that the symptoms of having too high LANOXIN doses may be difficult to recognize in infants and pediatric patients. Symptoms such as weight loss, failure to thrive in infants, abdominal pain, and behavioral disturbances may be indications of digoxin toxicity.•Instruct the patient to monitor and record their heart rate and blood pressure daily.

LANOXIN is registered trademark of GlaxoSmithKline.

Manufactured for
Covis Pharma
Zug, 6300 Switzerland

2025, Covis Pharma. All rights reserved.

PRINCIPAL DISPLAY PANEL - Adult Carton Label - Ampule

C O V I S

10 single-dose ampuls 2 mL each NDC 70515-260-10
Discard unused portion

LANOXIN®(digoxin) Injection
500 mcg/2 mL (250 mcg/mL)

For intravenous or intramuscular injection. Dilution not required.

In a vehicle of 42.5% (W/V) propylene glycol and 10% alcohol (V/V). Dibasic sodium
phosphate 0.17%, citric acid anhydrous 0.08%.

See prescribing information for dosage information.

Store at 25°C (77°F); excursions permitted to 15°C to 30°C (59°F to 86°F)
[see USP Controlled Room Temperature] and protect from light.

Manufactured for
Covis Pharma
Zug, 6300 Switzerland
Made in Germany
©2024, Covis Pharma

Rx only

PRINCIPAL DISPLAY PANEL - Adult Carton Label - Vial

C O V I S

NDC 70515-261-10

10 single-dose vials 2 mL each
Discard unused portion

LANOXIN®(digoxin) Injection

500 mcg/2 mL
(250 mcg/mL)

For Intravenous or Intramuscular Injection.
Dilution not required.

Rx only

NDC 70515-261-10
LANOXIN®(digoxin) Injection 500 mcg/2 mL (250 mcg/mL)

In a vehicle of 42.5% (W/V) propylene glycol and 10% alcohol (V/V).
Dibasic sodium phosphate 0.17%, citric acid anhydrous 0.08%.

See prescribing information for dosage information.

Store at 25°C (77°F); excursions permitted to 15°C to 30°C (59°F to 86°F)
[see USP Controlled Room Temperature] and protect from light.

Manufactured for
Covis Pharma
Zug, 6300 Switzerland

Made in Germany
©2024, Covis Pharma

PRINCIPAL DISPLAY PANEL - Pediatric Carton Label - Ampule

NDC 70515-262-10 10 single-dose ampules 1 mL each – Discard unused portion

LANOXIN®(digoxin) Injection
Pediatric

100 mcg/mL

For intravenous or intramuscular injection. Dilution not required. In a vehicle of 42.5% (W/V) propylene glycol
and 10% alcohol (V/V). Sodium phosphate 0.17%. Citric acid anhydrous 0.08%.

See prescribing information for dosage information.

Store at 25°C (77°F); excursions permitted to 15°C to 30°C (59°F to 86°F)
[see USP Controlled Room Temperature] and protect from light.

Rx only C O V I S

PRINCIPAL DISPLAY PANEL - Pediatric Carton Label - Vial

NDC 70515-263-10 10 vials 1 mL each – Discard unused portion Rx only

LANOXIN®(digoxin) Injection
Pediatric

100 mcg/mL

For Intravenous or Intramuscular Injection. Dilution not required. C O V I S

NDC 70515-263-10 10 single-dose vials 1 mL each

LANOXIN®(digoxin) Injection Pediatric
100 mcg/mL

In a vehicle of 42.5% (W/V) propylene glycol and 10% alcohol (V/V).
Sodium phosphate 0.17%. Citric acid anhydrous 0.08%.

See prescribing information for dosage information.

Store at 25°C (77°F); excursions permitted to 15°C to 30°C (59°F to 86°F)
[see USP Controlled Room Temperature] and protect from light.

Manufactured for
Covis Pharma
Zug, 6300 Switzerland

Made in Germany
©2024, Covis Pharma